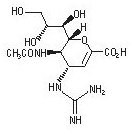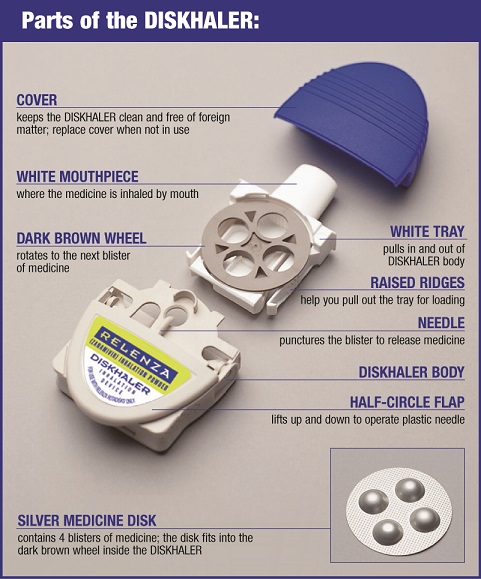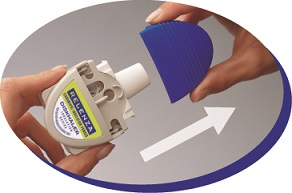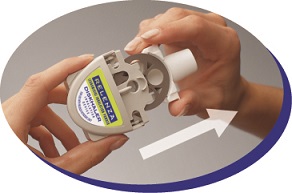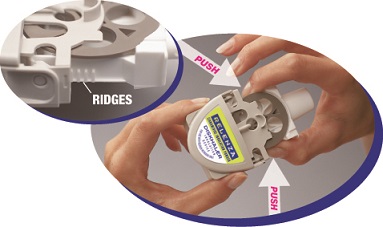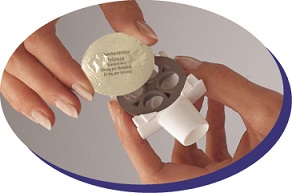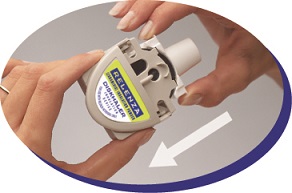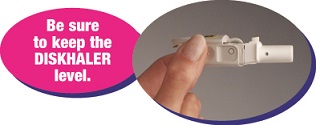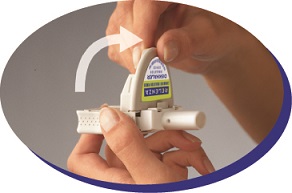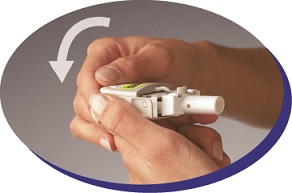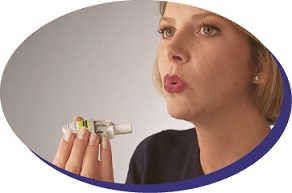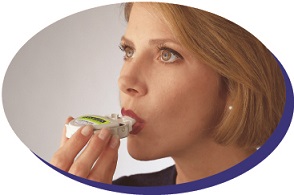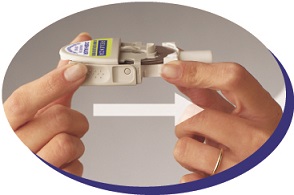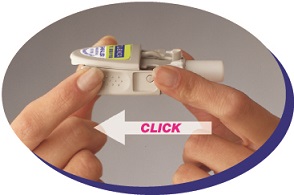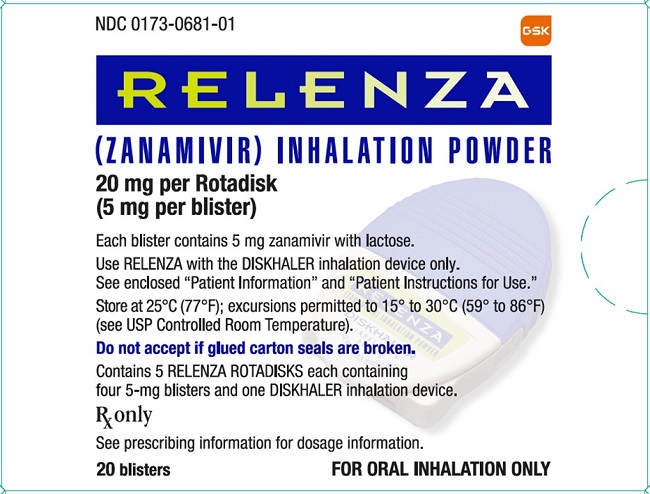 DRUG LABEL: RELENZA
NDC: 0173-0681 | Form: POWDER
Manufacturer: GlaxoSmithKline LLC
Category: prescription | Type: HUMAN PRESCRIPTION DRUG LABEL
Date: 20231024

ACTIVE INGREDIENTS: ZANAMIVIR 5 mg/1 1
INACTIVE INGREDIENTS: LACTOSE, UNSPECIFIED FORM

HIGHLIGHTS OF PRESCRIBING INFORMATION

These highlights do not include all the information needed to use RELENZA safely and effectively. See full prescribing information for RELENZA.
RELENZA (zanamivir inhalation powder), for oral inhalation use
Initial U.S. Approval: 1999

1 INDICATIONS AND USAGE

RELENZA, an influenza virus neuraminidase inhibitor (NAI), is indicated for:

Treatment of acute, uncomplicated influenza type A and B infections in patients aged 7 years and older who have been symptomatic for no more than 2 days. (1.1)

Prophylaxis of influenza in patients aged 5 years and older. (1.2)

Important Limitations of Use:

Not recommended for treatment or prophylaxis of influenza in:

- Individuals with underlying airways disease. (5.1)

Not proven effective for:

- Treatment in individuals with underlying airways disease. (1.3)
- Prophylaxis in nursing home residents. (1.3)

Not a substitute for annual influenza vaccination. (1.3)

Consider available information on influenza drug susceptibility patterns and treatment effects when deciding whether to use RELENZA. (1.3)

2 DOSAGE AND ADMINISTRATION

Indication | Dose
Treatment of Influenza (2.2) | 10 mg twice daily for 5 days
Prophylaxis: (2.3)
Household Setting | 10 mg once daily for 10 days
Community Outbreaks | 10 mg once daily for 28 days

Note: The 10-mg dose is provided by 2 inhalations (one 5-mg blister per inhalation). (2.1)

3 DOSAGE FORMS AND STRENGTHS

Blister for oral inhalation: 5 mg. Four 5-mg blisters of powder on a ROTADISK for oral inhalation via DISKHALER. Packaged in carton containing 5 ROTADISKs (total of 10 doses) and 1 DISKHALER inhalation device. (3)

4 CONTRAINDICATIONS

Do not use in patients with history of allergic reaction to any ingredient of RELENZA, including milk proteins. (4)

5 WARNINGS AND PRECAUTIONS

- Bronchospasm: Serious, sometimes fatal, cases have occurred. Not recommended in individuals with underlying airways disease. Discontinue RELENZA if bronchospasm or decline in respiratory function develops. (5.1)
- Allergic Reactions: Discontinue RELENZA and initiate appropriate treatment if an allergic reaction occurs or is suspected. (5.2)
- Neuropsychiatric Events: Patients with influenza, particularly pediatric patients, may be at an increased risk of seizures, confusion, or abnormal behavior early in their illness. Monitor for signs of abnormal behavior. (5.3)
- High-Risk Underlying Medical Conditions: Safety and effectiveness have not been demonstrated in these patients. (5.4)

6 ADVERSE REACTIONS

The most common adverse events reported in greater than 1.5% of subjects treated with RELENZA and more commonly than in subjects treated with placebo are:

- Treatment Trials – sinusitis, dizziness. (6.1)
- Prophylaxis Trials – fever and/or chills, arthralgia, and articular rheumatism. (6.1)

To report SUSPECTED ADVERSE REACTIONS, contact GlaxoSmithKline at 1-888-825-5249 or FDA at 1-800-FDA-1088 or www.fda.gov/medwatch.

7 DRUG INTERACTIONS

Live attenuated influenza vaccine, intranasal (7):

- Do not administer until 48 hours following cessation of RELENZA.
- Do not administer RELENZA until 2 weeks following administration of the live attenuated influenza vaccine, unless medically indicated.

FULL PRESCRIBING INFORMATION

1 INDICATIONS AND USAGE

1.1 Treatment of Influenza

RELENZA (zanamivir) inhalation powder is indicated for treatment of uncomplicated acute illness due to influenza A and B virus in adults and pediatric patients aged 7 years and older who have been symptomatic for no more than 2 days.

1.2 Prophylaxis of Influenza

RELENZA is indicated for prophylaxis of influenza in adults and pediatric patients aged 5 years and older.

1.3 Important Limitations of Use

- RELENZA is not recommended for treatment or prophylaxis of influenza in individuals with underlying airways disease (such as asthma or chronic obstructive pulmonary disease) due to risk of serious bronchospasm [see Warnings and Precautions (5.1)].
- RELENZA has not been proven effective for treatment of influenza in individuals with underlying airways disease.
- RELENZA has not been proven effective for prophylaxis of influenza in the nursing home setting.
- RELENZA is not a substitute for early influenza vaccination on an annual basis as recommended by the Centers for Disease Control's Immunization Practices Advisory Committee.
- Influenza viruses change over time. Emergence of resistance mutations could decrease drug effectiveness. Other factors (for example, changes in viral virulence) might also diminish clinical benefit of antiviral drugs. Prescribers should consider available information on influenza drug susceptibility patterns and treatment effects when deciding whether to use RELENZA.
- There is no evidence for efficacy of zanamivir in any illness caused by agents other than influenza virus A and B.
- Patients should be advised that the use of RELENZA for treatment of influenza has not been shown to reduce the risk of transmission of influenza to others.

2 DOSAGE AND ADMINISTRATION

2.1 Dosing Considerations

- RELENZA is for administration to the respiratory tract by oral inhalation only, using the DISKHALER device provided [see Warnings and Precautions (5.6)].
- The 10-mg dose is provided by 2 inhalations (one 5-mg blister per inhalation).
- Patients should be instructed in the use of the delivery system. Instructions should include a demonstration whenever possible. If RELENZA is prescribed for children, it should be used only under adult supervision and instruction, and the supervising adult should first be instructed by a healthcare professional [see Patient Counseling Information (17)].
- Patients scheduled to use an inhaled bronchodilator at the same time as RELENZA should use their bronchodilator before taking RELENZA [see Patient Counseling Information (17)].

2.2 Treatment of Influenza

- The recommended dose of RELENZA for treatment of influenza in adults and pediatric patients aged 7 years and older is 10 mg twice daily (approximately 12 hours apart) for 5 days.
- Two doses should be taken on the first day of treatment whenever possible provided there is at least 2 hours between doses.
- On subsequent days, doses should be about 12 hours apart (e.g., morning and evening) at approximately the same time each day.
- The safety and efficacy of repeated treatment courses have not been studied.

2.3 Prophylaxis of Influenza

Household Setting

- The recommended dose of RELENZA for prophylaxis of influenza in adults and pediatric patients aged 5 years and older in a household setting is 10 mg once daily for 10 days.
- The dose should be administered at approximately the same time each day.
- There are no data on the effectiveness of prophylaxis with RELENZA in a household setting when initiated more than 1.5 days after the onset of signs or symptoms in the index case.

Community Outbreaks

- The recommended dose of RELENZA for prophylaxis of influenza in adults and adolescents in a community setting is 10 mg once daily for 28 days.
- The dose should be administered at approximately the same time each day.
- There are no data on the effectiveness of prophylaxis with RELENZA in a community outbreak when initiated more than 5 days after the outbreak was identified in the community.
- The safety and effectiveness of prophylaxis with RELENZA have not been evaluated for longer than 28 days’ duration.

3 DOSAGE FORMS AND STRENGTHS

Blister for oral inhalation: 5 mg. Four 5-mg blisters of powder on a ROTADISK for oral inhalation via DISKHALER. Packaged in carton containing 5 ROTADISKs (total of 10 doses) and 1 DISKHALER inhalation device [see How Supplied/Storage and Handling (16)].

4 CONTRAINDICATIONS

RELENZA is contraindicated in patients with history of allergic reaction to any ingredient of RELENZA, including milk proteins [see Warnings and Precautions (5.2), Description (11)].

5 WARNINGS AND PRECAUTIONS

5.1 Bronchospasm

RELENZA is not recommended for treatment or prophylaxis of influenza in individuals with underlying airways disease (such as asthma or chronic obstructive pulmonary disease).

Serious cases of bronchospasm, including fatalities, have been reported during treatment with RELENZA in patients with and without underlying airways disease. Many of these cases were reported during postmarketing and causality was difficult to assess.

RELENZA should be discontinued in any patient who develops bronchospasm or decline in respiratory function; immediate treatment and hospitalization may be required.

Some patients without prior pulmonary disease may also have respiratory abnormalities from acute respiratory infection that could resemble adverse drug reactions or increase patient vulnerability to adverse drug reactions.

Bronchospasm was documented following administration of zanamivir in 1 of 13 subjects with mild or moderate asthma (but without acute influenza‑like illness) in a Phase 1 trial. In a Phase 3 trial in subjects with acute influenza‑like illness superimposed on underlying asthma or chronic obstructive pulmonary disease, 10% (24 of 244) of subjects on zanamivir and 9% (22 of 237) on placebo experienced a greater than 20% decline in forced expiratory volume in 1 second (FEV1) following treatment for 5 days.

If use of RELENZA is considered for a patient with underlying airways disease, the potential risks and benefits should be carefully weighed. If a decision is made to prescribe RELENZA for such a patient, this should be done only under conditions of careful monitoring of respiratory function, close observation, and appropriate supportive care, including availability of fast‑acting bronchodilators.

5.2 Allergic Reactions

Allergic-like reactions, including oropharyngeal edema, serious skin rashes, and anaphylaxis have been reported in postmarketing experience with RELENZA. RELENZA should be stopped and appropriate treatment instituted if an allergic reaction occurs or is suspected.

5.3 Neuropsychiatric Events

Influenza can be associated with a variety of neurologic and behavioral symptoms which can include events such as seizures, hallucinations, delirium, and abnormal behavior, in some cases resulting in fatal outcomes. These events may occur in the setting of encephalitis or encephalopathy but can occur without obvious severe disease.

There have been postmarketing reports of delirium and abnormal behavior leading to injury in patients with influenza who were receiving neuraminidase inhibitors (NAIs), including RELENZA. Because these events were reported voluntarily during clinical practice, estimates of frequency cannot be made, but they appear to be uncommon based on usage data for RELENZA. These events were reported primarily among pediatric patients and often had an abrupt onset and rapid resolution. The contribution of RELENZA to these events has not been established. Patients with influenza should be closely monitored for signs of abnormal behavior. If neuropsychiatric symptoms occur, the risks and benefits of continuing treatment should be evaluated for each patient.

5.4 Limitations of Populations Studied

Safety and efficacy have not been demonstrated in patients with high-risk underlying medical conditions. No information is available regarding treatment of influenza in patients with any medical condition sufficiently severe or unstable to be considered at imminent risk of requiring inpatient management.

5.5 Bacterial Infections

Serious bacterial infections may begin with influenza-like symptoms or may coexist with or occur as complications during the course of influenza. RELENZA has not been shown to prevent such complications.

5.6 Importance of Proper Route of Administration

RELENZA inhalation powder must not be made into an extemporaneous solution for administration by nebulization or mechanical ventilation. There have been reports of hospitalized patients with influenza who received a solution made with RELENZA inhalation powder administered by nebulization or mechanical ventilation, including a fatal case where it was reported that the lactose in this formulation obstructed the proper functioning of the equipment. RELENZA inhalation powder must only be administered using the device provided [see Dosage and Administration (2.1)].

5.7 Importance of Proper Use of DISKHALER

Effective and safe use of RELENZA requires proper use of the DISKHALER to inhale the drug. Prescribers should carefully evaluate the ability of young children to use the delivery system if use of RELENZA is considered [see Use in Specific Populations (8.4)].

6 ADVERSE REACTIONS

The following adverse reactions are discussed in greater detail in other sections of the labeling:

- Bronchospasm [see Warnings and Precautions (5.1)].
- Safety information in patients with underlying airways disease [see Warnings and Precautions (5.1)].
- Allergic-like reactions [see Warnings and Precautions (5.2)].

6.1 Clinical Trials Experience

Because clinical trials are conducted under widely varying conditions, adverse reaction rates observed in the clinical trials of a drug cannot be directly compared with rates in the clinical trials of another drug and may not reflect the rates observed in practice.

The placebo used in clinical trials consisted of inhaled lactose powder, which is also the vehicle for the active drug; therefore, some adverse events occurring at similar frequencies in different treatment groups could be related to lactose vehicle inhalation.

Treatment of Influenza

Clinical Trials in Adults and Adolescents: Adverse events that occurred with an incidence greater than or equal to 1.5% in treatment trials are listed in Table 1. This table shows adverse events occurring in subjects aged 12 years and older receiving RELENZA 10 mg inhaled twice daily, RELENZA in all inhalation regimens, and placebo inhaled twice daily (where placebo consisted of the same lactose vehicle used in RELENZA).

Table 1. Summary of Adverse Events ≥1.5% Incidence during Treatment in Adults and Adolescents
Adverse Event | RELENZA |  | Placebo; (Lactose Vehicle); (n = 1,520)
Adverse Event | 10 mg b.i.d. Inhaled; (n = 1,132) | All Dosing Regimensa; (n = 2,289) | Placebo; (Lactose Vehicle); (n = 1,520)
Body as a whole
Headaches | 2% | 2% | 3%
Digestive
Diarrhea | 3% | 3% | 4%
Nausea | 3% | 3% | 3%
Vomiting | 1% | 1% | 2%
Respiratory
Nasal signs and symptoms | 2% | 3% | 3%
Bronchitis | 2% | 2% | 3%
Cough | 2% | 2% | 3%
Sinusitis | 3% | 2% | 2%
Ear, nose, and throat infections | 2% | 1% | 2%
Nervous system
Dizziness | 2% | 1% | <1%
a Includes trials where RELENZA was administered intranasally (6.4 mg 2 to 4 times per day in addition to inhaled preparation) and/or inhaled more frequently (q.i.d.) than the currently recommended dose.

Additional adverse reactions occurring in less than 1.5% of subjects receiving RELENZA included malaise, fatigue, fever, abdominal pain, myalgia, arthralgia, and urticaria.

The most frequent laboratory abnormalities in Phase 3 treatment trials included elevations of liver enzymes and creatine phosphokinase (CPK), lymphopenia, and neutropenia. These were reported in similar proportions of zanamivir and lactose vehicle placebo recipients with acute influenza‑like illness.

Clinical Trials in Pediatric Subjects: Adverse events that occurred with an incidence greater than or equal to 1.5% in children receiving treatment doses of RELENZA in 2 Phase 3 trials are listed in Table 2. This table shows adverse events occurring in pediatric subjects aged 5 to 12 years receiving RELENZA 10 mg inhaled twice daily and placebo inhaled twice daily (where placebo consisted of the same lactose vehicle used in RELENZA).

Table 2. Summary of Adverse Events ≥1.5% Incidence during Treatment in Pediatric Subjectsa
Adverse Event | RELENZA; 10 mg b.i.d. Inhaled; (n = 291) | Placebo; (Lactose Vehicle); (n = 318)
Respiratory
Ear, nose, and throat infections | 5% | 5%
Ear, nose, and throat hemorrhage | <1% | 2%
Asthma | <1% | 2%
Cough | <1% | 2%
Digestive
Vomiting | 2% | 3%
Diarrhea | 2% | 2%
Nausea | <1% | 2%
a Includes a subset of subjects receiving RELENZA for treatment of influenza in a prophylaxis trial.

In 1 of the 2 trials described in Table 2, some additional information is available from children (aged 5 to 12 years) without acute influenza-like illness who received an investigational prophylaxis regimen of RELENZA; 132 children received RELENZA and 145 children received placebo. Among these children, nasal signs and symptoms (zanamivir 20%, placebo 9%), cough (zanamivir 16%, placebo 8%), and throat/tonsil discomfort and pain (zanamivir 11%, placebo 6%) were reported more frequently with RELENZA than placebo. In a subset with chronic pulmonary disease, lower respiratory adverse events (described as asthma, cough, or viral respiratory infections which could include influenza-like symptoms) were reported in 7 of 7 zanamivir recipients and 5 of 12 placebo recipients.

Prophylaxis of Influenza

Family/Household Prophylaxis Trials: Adverse events that occurred with an incidence of greater than or equal to 1.5% in the 2 prophylaxis trials are listed in Table 3. This table shows adverse events occurring in subjects aged 5 years and older receiving RELENZA 10 mg inhaled once daily for 10 days.

Table 3. Summary of Adverse Events ≥1.5% Incidence during 10-Day Prophylaxis Trials in Adults, Adolescents, and Childrena
Adverse Event | Contact Cases
Adverse Event | RELENZA; (n = 1,068) | Placebo; (n = 1,059)
Lower respiratory
Viral respiratory infections | 13% | 19%
Cough | 7% | 9%
Neurologic
Headaches | 13% | 14%
Ear, nose, and throat
Nasal signs and symptoms | 12% | 12%
Throat and tonsil discomfort and pain | 8% | 9%
Nasal inflammation | 1% | 2%
Musculoskeletal
Muscle pain | 3% | 3%
Endocrine and metabolic
Feeding problems (decreased or increased appetite and anorexia) | 2% | 2%
Gastrointestinal
Nausea and vomiting | 1% | 2%
Non-site specific
Malaise and fatigue | 5% | 5%
Temperature regulation disturbances (fever and/or chills) | 5% | 4%
a In prophylaxis trials, symptoms associated with influenza-like illness were captured as adverse events; subjects were enrolled during a winter respiratory season during which time any symptoms that occurred were captured as adverse events.

Community Prophylaxis Trials: Adverse events that occurred with an incidence of greater than or equal to 1.5% in 2 prophylaxis trials are listed in Table 4. This table shows adverse events occurring in subjects aged 5 years and older receiving RELENZA 10 mg inhaled once daily for 28 days.

Table 4. Summary of Adverse Events ≥1.5% Incidence during 28-Day Prophylaxis Trials in Adults, Adolescents, and Childrena
Adverse Event | RELENZA; (n = 2,231) | Placebo; (n = 2,239)
Neurologic
Headaches | 24% | 26%
Ear, nose, and throat
Throat and tonsil discomfort and pain | 19% | 20%
Nasal signs and symptoms | 12% | 13%
Ear, nose, and throat infections | 2% | 2%
Lower respiratory
Cough | 17% | 18%
Viral respiratory infections | 3% | 4%
Musculoskeletal
Muscle pain | 8% | 8%
Musculoskeletal pain | 6% | 6%
Arthralgia and articular rheumatism | 2% | <1%
Endocrine and metabolic
Feeding problems (decreased or increased appetite and anorexia) | 4% | 4%
Gastrointestinal
Nausea and vomiting | 2% | 3%
Diarrhea | 2% | 2%
Non-site specific
Temperature regulation disturbances (fever and/or chills) | 9% | 10%
Malaise and fatigue | 8% | 8%
a In prophylaxis trials, symptoms associated with influenza-like illness were captured as adverse events; subjects were enrolled during a winter respiratory season during which time any symptoms that occurred were captured as adverse events.

6.2 Postmarketing Experience

The following adverse reactions have been identified during postapproval use of RELENZA. Because these reactions are reported voluntarily from a population of uncertain size, it is not always possible to reliably estimate their frequency or establish a causal relationship to drug exposure.

Allergic Reactions

Allergic or allergic-like reaction, including oropharyngeal edema [see Warnings and Precautions (5.2)].

Psychiatric

Delirium, including symptoms such as altered level of consciousness, confusion, abnormal behavior, delusions, hallucinations, agitation, anxiety, nightmares [see Warnings and Precautions (5.3)].

Cardiac

Arrhythmias, syncope.

Neurologic

Seizures. Vasovagal-like episodes have been reported shortly following inhalation of zanamivir.

Respiratory

Bronchospasm, dyspnea [see Warnings and Precautions (5.1)].

Skin

Facial edema; rash, including serious cutaneous reactions (e.g., erythema multiforme, Stevens-Johnson syndrome, toxic epidermal necrolysis); urticaria [see Warnings and Precautions (5.2)].

7 DRUG INTERACTIONS

The concurrent use of RELENZA with live attenuated influenza vaccine (LAIV) intranasal has not been evaluated. However, because of potential interference between these products, LAIV should not be administered within 2 weeks before or 48 hours after administration of RELENZA, unless medically indicated. The concern about possible interference arises from the potential for antiviral drugs to inhibit replication of live vaccine virus.

Trivalent inactivated influenza vaccine can be administered at any time relative to use of RELENZA [see Microbiology (12.4)].

8 USE IN SPECIFIC POPULATIONS

8.1 Pregnancy

Risk Summary

Available data from published studies suggest that use of RELENZA during pregnancy is not associated with an increased risk of birth defects or adverse maternal or fetal outcomes. However, these studies are limited by their small sample sizes, which preclude a definitive assessment of the risk (see Data). There are risks to the mother and fetus associated with influenza infection in pregnancy (see Clinical Considerations). In animal reproduction studies, no adverse developmental effects were observed with intravenous or subcutaneous administration of zanamivir at exposures 300 and 150 times, respectively, the systemic exposure at the maximum recommended human inhalation dose (MRHID) of 10 mg twice daily (see Data).

The background risk of major birth defects and miscarriage for the indicated population is unknown. All pregnancies have a background risk of birth defect, loss, or other adverse outcomes. In the U.S. general population, the background risk of major birth defects and miscarriage in clinically recognized pregnancies is 2% to 4% and 15% to 20%, respectively.

Clinical Considerations

Disease-Associated Maternal and/or Embryo/Fetal Risk: Pregnant women are at higher risk of severe complications from influenza, which may lead to adverse pregnancy and/or fetal outcomes, including maternal death, stillbirths, birth defects, preterm delivery, low birth weight, and small for gestational age.

Data

Human Data: A study of population-based registers from Denmark, Norway, Sweden, and France reported outcomes of 5,824 pregnant women who filled a prescription for an NAI compared with outcomes in unexposed pregnant women in the general population. This study included 1,560 women who filled a prescription for zanamivir (including 321 first trimester exposures). Although no specific analyses were conducted for zanamivir, exposure to the NAI class in utero was not associated with major birth defects, preterm birth, low birth weight, small for gestational age, still birth, neonatal morbidity, or neonatal mortality.

A few published studies compared outcomes of pregnant women exposed to zanamivir with outcomes in various comparator cohorts. These studies suggested no increased risk of major birth defects, preterm birth, or low birth weight. Sample sizes in these studies ranged from 50 to 180 pregnant women exposed to zanamivir, including 15 to 44 women exposed in the first trimester. Limitations of available studies include the lack of specific analyses for zanamivir, possible exposure and outcome misclassification, and small sample sizes. These limitations preclude a definitive assessment of the risk.

Animal Data: Zanamivir was administered intravenously to pregnant rats and rabbits at 1, 9, or 90 mg/kg/day during organogenesis (gestation Day 6 to 15 [rat] and 7 to 19 [rabbit]). No adverse maternal or embryo-fetal effects were observed up to the highest intravenous dose of zanamivir (90 mg/kg/day), resulting in systemic drug exposure (AUC) estimated from both rats and rabbits, 300 times the exposure at the MRHID. In a separate study, zanamivir was administered subcutaneously to pregnant rats at 3, 27, and 240 mg/kg/day in three divided doses during organogenesis (gestation Day 7 to 17). An increased incidence of skeletal and visceral alterations and variants was observed at the high dose (240 mg/kg/day). No adverse maternal or embryo-fetal effects were observed at the middle dose (27 mg/kg/day), resulting in systemic drug exposure (AUC) 150 times the exposure at the MRHID.

In prenatal and postnatal development studies in rats, zanamivir was administered intravenously at 1, 9, or 90 mg/kg/day during organogenesis (gestation Day 0 to 19) or from late gestation through delivery and lactation (gestation Day 16 to post-partum/lactation Day 21). No significant effects were observed in the offspring at systemic drug exposures (AUC) estimated to be 300 times the exposure at the MRHID.

Zanamivir distributed across the placenta in pregnant rats and rabbits, with less than 0.04% of the administered maternal dose being recovered from the fetus on gestation Day 12.

8.2 Lactation

Risk Summary

There are no data on the presence of zanamivir in human milk or the effects on milk production. There are data from adults that have shown low oral bioavailability of zanamivir. Limited data from postmarketing case reports have not suggested a safety concern in infants exposed to breast milk of mothers using RELENZA. Zanamivir was present in the milk of lactating rats without effect on nursing pups (see Data). The developmental and health benefits of breastfeeding should be considered along with the mother’s clinical need for RELENZA and any potential adverse effects on the breastfed child from RELENZA or the underlying maternal condition.

Data

In a lactation study, zanamivir was excreted in the milk of lactating rats administered zanamivir intravenously (10 mg/kg) on post-partum/lactation Day 10, with peak milk concentrations of approximately 10% that of maternal plasma concentrations occurring 30 minutes post-dose. No effects of zanamivir on growth and postnatal development were observed in nursing pups at the highest intravenous dose tested in rats. Maternal systemic exposure (AUC) of zanamivir was approximately 300 times the exposure in humans at the MRHID.

8.4 Pediatric Use

Treatment of Influenza

Safety and effectiveness of RELENZA for treatment of influenza have not been assessed in pediatric patients younger than 7 years, but were studied in a Phase 3 treatment trial in pediatric subjects, where 471 children aged 5 to 12 years received zanamivir or placebo [see Clinical Studies (14.1)]. Adolescents were included in the 3 principal Phase 3 adult treatment trials. In these trials, 67 patients were aged 12 to 16 years. No definite differences in safety and efficacy were observed between these adolescent patients and young adults.

In a Phase 1 trial of 16 children aged 6 to 12 years with signs and symptoms of respiratory disease, 4 did not produce a measurable peak inspiratory flow rate (PIFR) through the DISKHALER (3 with no adequate inhalation on request, 1 with missing data), 9 had measurable PIFR on each of 2 inhalations, and 3 achieved measurable PIFR on only 1 of 2 inhalations. Neither of two 6-year-olds and one of two 7-year-olds produced measurable PIFR. Overall, 8 of the 16 children (including all those younger than 8 years) either did not produce measurable inspiratory flow through the DISKHALER or produced peak inspiratory flow rates below the 60 L/minute considered optimal for the device under standardized in vitro testing; lack of measurable flow rate was related to low or undetectable serum concentrations [see Clinical Pharmacology (12.3), Clinical Studies (14.1)]. Prescribers should carefully evaluate the ability of young children to use the delivery system if prescription of RELENZA is considered.

Prophylaxis of Influenza

The safety and effectiveness of RELENZA for prophylaxis of influenza have been studied in 4 Phase 3 trials where 273 children aged 5 to 11 years and 239 adolescents aged 12 to 16 years received RELENZA. No differences in safety and effectiveness were observed between pediatric and adult subjects [see Clinical Studies (14.2)].

8.5 Geriatric Use

Of the total number of subjects in 6 clinical trials of RELENZA for treatment of influenza, 59 subjects were aged 65 years and older, while 24 subjects were aged 75 years and older. Of the total number of subjects in 4 clinical trials of RELENZA for prophylaxis of influenza in households and community settings, 954 subjects were aged 65 years and older, while 347 subjects were aged 75 years and older. No overall differences in safety or effectiveness were observed between these subjects and younger subjects, and other reported clinical experience has not identified differences in responses between the elderly and younger subjects, but greater sensitivity of some older individuals cannot be ruled out. Elderly patients may need assistance with use of the device.

In 2 additional trials of RELENZA for prophylaxis of influenza in the nursing home setting, efficacy was not demonstrated [see Indications and Usage (1.3)].

8.6 Renal Impairment

Safety and efficacy have not been documented in the presence of severe renal insufficiency. Due to the low systemic bioavailability of zanamivir following oral inhalation, no dosage adjustments are necessary in patients with renal impairment. However, the potential for drug accumulation should be considered.

10 OVERDOSAGE

Reports of overdosage from administration of RELENZA have been received during postmarketing experience. The reported clinical signs or symptoms were similar to those observed with therapeutic doses of RELENZA and the underlying disease.

As zanamivir has a low molecular weight, low protein binding, and small volume of distribution, it is expected to be removed by hemodialysis.

11 DESCRIPTION

The active component of RELENZA is zanamivir. The chemical name of zanamivir is 5-(acetylamino)-4-[(aminoiminomethyl)-amino]-2,6-anhydro-3,4,5-trideoxy-D-glycero-D-galacto-non-2-enonic acid. It has a molecular formula of C12H20N4O7 and a molecular weight of 332.3. It has the following structural formula:

Zanamivir is a white to off-white powder for oral inhalation with a solubility of approximately 18 mg/mL in water at 20°C.

RELENZA is for administration to the respiratory tract by oral inhalation only. Each RELENZA ROTADISK contains 4 regularly spaced double-foil blisters with each blister containing a powder mixture of 5 mg of zanamivir and 20 mg of lactose (which contains milk proteins). The contents of each blister are inhaled using a specially designed breath-activated plastic device for inhaling powder called the DISKHALER. After a RELENZA ROTADISK is loaded into the DISKHALER, a blister that contains medication is pierced and the zanamivir is dispersed into the air stream created when the patient inhales through the mouthpiece. The amount of drug delivered to the respiratory tract will depend on patient factors such as inspiratory flow. Under standardized in vitro testing, RELENZA ROTADISK delivers 4 mg of zanamivir from the DISKHALER device when tested at a pressure drop of 3 kPa (corresponding to a flow rate of about 62 to 65 L/minute) for 3 seconds.

12 CLINICAL PHARMACOLOGY

12.1 Mechanism of Action

Zanamivir is an antiviral drug with activity against influenza virus [see Microbiology (12.4)].

12.2 Pharmacodynamics

Cardiac Electrophysiology

In a thorough QT/QTc study in 40 healthy subjects, intravenous zanamivir 600 mg and 1,200 mg (60 and 120 times the dose in RELENZA) had no effect on the QTc interval and did not prolong the PR interval.

12.3 Pharmacokinetics

Absorption and Bioavailability

Pharmacokinetic studies of orally inhaled zanamivir indicate that approximately 4% to 17% of the inhaled dose is systemically absorbed. The peak serum concentrations ranged from 17 to 142 ng/mL within 1 to 2 hours following a 10‑mg dose. The area under the serum concentration versus time curve (AUC∞) ranged from 111 to 1,364 ng•hour/mL.

Distribution

Zanamivir plasma protein binding is less than 10% and the blood to plasma ratio is 0.56. The volume of distribution is approximately 16 L. The 2 major sites of deposition are the oropharynx and the lungs (mean 77.6% and 13.2%, respectively).

Elimination

The serum half‑life of zanamivir following administration by oral inhalation ranges from 2.5 to 5.1 hours.

Metabolism: No metabolites have been detected in humans.

Excretion: Zanamivir is eliminated by renal filtration with excretion of a single dose completed within 24 hours. Total clearance ranges from 2.5 to 10.9 L/hour. Unabsorbed drug is excreted in the feces.

Specific Populations

Patients with Hepatic Impairment: The pharmacokinetics of zanamivir have not been studied in patients with impaired hepatic function.

Patients with Renal Impairment: After a single intravenous dose of 4 mg or 2 mg of zanamivir in volunteers with renal impairment determined by the Cockcroft and Gault method, significant increases in systemic exposure were observed (Table 5).

Table 5. Zanamivir Exposure in Subjects with Renal Impairment Compared with Healthy Subjects
 | CrCl >70 mL/min (n = 7) | CrCl = 25-70 mL/min (n = 5) | CrCl <25 mL/min (n = 5)
Cmax (ng/mL)a | 257 (182, 363) | 316 (234, 427) | 202 (141, 289)
AUC0-inf (ng∙h/mL)a | 737 (567, 957) | 1,519 (1181, 1954) | 2,587 (1514, 4419)
Cmax = Maximum serum concentration; AUC0-inf = Area under the serum concentration-time curve from zero to infinity; CrCl = Creatinine Clearance.
a Geometric mean (95% confidence interval).

Pediatric Patients: The pharmacokinetics of zanamivir were evaluated in pediatric subjects with signs and symptoms of respiratory illness. Sixteen subjects, aged 6 to 12 years, received a single dose of 10 mg zanamivir dry powder via DISKHALER. Five subjects had either undetectable zanamivir serum concentrations or had low drug concentrations (8.32 to 10.38 ng/mL) that were not detectable after 1.5 hours. Eleven subjects had Cmax median values of 43 ng/mL (range: 15 to 74) and AUC∞ median values of 167 ng•hour/mL (range: 58 to 279). Low or undetectable serum concentrations were related to lack of measurable PIFR in individual subjects [see Use in Specific Populations (8.4), Clinical Studies (14.1)].

Geriatric Patients: The pharmacokinetics of zanamivir have not been studied in subjects older than 65 years [see Use in Specific Populations (8.5)].

Gender, Race, and Weight: There were no clinically significant pharmacokinetic changes associated with gender, race, or weight.

Drug Interaction Studies

Zanamivir is not a substrate of cytochrome P450 (CYP) isoenzymes or P-glycoprotein (P-gp), does not inhibit renal transporters OAT1-4, OCT1-3, or URAT1, and does not inhibit CYP isoenzymes CYP1A1/2, 2A6, 2C9, 2C19, 2D6, 2E1, and 3A4 in human liver microsomes.

12.4 Microbiology

Mechanism of Action

Zanamivir is an inhibitor of influenza virus neuraminidase (NA), an enzyme that releases viral particles from the plasma membrane of infected cells and promotes virus spread in the respiratory tract. In neuraminidase inhibition assays, zanamivir is active against all NA enzyme subtypes N1 to N9. The median baseline 50% neuraminidase inhibitory concentrations (IC50) of zanamivir for influenza type A subtype H1N1, influenza type A subtype H3N2, and influenza type B viruses were 0.85 nM (n = 31; range: 0.45 to 1.35 nM), 1.01 nM (n = 32; range: 0.33 to 2.04 nM), and 3.86 nM (n = 16; range: 2.02 to 5.77 nM), respectively, in a chemiluminescent assay. Amino acid substitutions have been found in the neuraminidase active site that reduce virus susceptibility to zanamivir (see Resistance).

Antiviral Activity

Zanamivir has been demonstrated to inhibit laboratory and clinical isolates of influenza virus in cell culture. The median EC50 values of zanamivir in cell culture assays for influenza type A (subtypes H1N1 and H3N2) and influenza type B viruses were 210 nM (70 ng/mL) (n = 10; range: 1 to 16,000 nM), 14 nM (4.7 ng/mL) (n = 12; range: 1 to 1,700 nM), and 18 nM (6 ng/mL) (n = 9; range: 3 to 1,300 nM), respectively. The relationship between the cell culture inhibition of influenza virus by zanamivir and the inhibition of influenza virus replication in humans has not been established.

Resistance

Cell Culture: Influenza viruses with reduced susceptibility to zanamivir have been selected in cell culture by multiple passages of the virus in the presence of increasing concentrations of the drug. Reduced susceptibility of influenza virus to inhibition by zanamivir may be conferred by amino acid substitutions in the viral NA and/or hemagglutinin (HA) proteins (Table 6).

Table 6: Amino Acid Substitutions Selected by Zanamivir in Cell Culture Studies
Protein | Type/Subtype
Protein | A/H1N1a | A/H3N2b | Bc
NA | D199G | T148I | E117D/G
HAd | G155E, A197T | -- | V90A, N145S, N150S, Q226K, L239Q
NA = Neuraminidase; HA = Hemagglutinin.
a Numbering based on A/California/04/2009.
b Numbering based on A/Texas/50/2012.
c Numbering based on B/Massachusetts/02/2012.
d HA numbering begins after the predicted signal peptide.

Clinical: Influenza viruses with amino acid substitutions and deletions associated with reduced susceptibility to zanamivir have been identified in patients treated with zanamivir and in circulating viruses from untreated individuals. Genetic analysis of these viruses showed that the reduced susceptibility to zanamivir is associated with mutations that result in amino acid changes in the viral NA or viral HA or both (see Table 7). The clinical impact of substitutions that reduce virus susceptibility to zanamivir is variable and may be strain-dependent.

Table 7: Amino Acid Substitutions Observed in Virus from Humans and Associated with Reduced Susceptibility to Zanamivir
Protein | Type/Subtype
Protein | A/H1N1a | A/H3N2b | Bc
NA | N70S, S110F, V116A, I117R, E119Dd/Gd/Kd, H126N, Q136Ke, T148A, D151Ge+H275Y, R152K, Y155H, D199Y, I223K/Rd/T, S247I/R, G249R, I267V, Q313R, N325K, R368Gd, G370Dd, I427T, N434Sd, G460S | E119I/V, Q136Ke, D151A/Ge/V, V165I+H274N, G248R+K249E, N294Sd, V303I, G320R, T325Id, N329K/R, S333G, N342K, Q391K, D463N | P76S, G104E, E105K, T106L+P165L, G108E, P124T, H134N/Q/R, Q138R, P139S, G140R, G145R, R150Kd, R154K, K186R+I262T, D197E/N/Y, A200T, I221L/N/Td, G243D/S, A245T, S246P, G247D+I361V, S249G/N, I348T/V, R374K, L396H, G407S, H431R, W438R
HAf | L151Pd, V152I, S162N, S183P, A197T, D222G | R142Gd, N225D | T198Id
NA = Neuraminidase; HA = Hemagglutinin.
a Numbering based on A/California/04/2009.
b Numbering based on A/Texas/50/2012.
c Numbering based on B/Massachusetts/02/2012.
d Emerged in patients treated with zanamivir.
e Possible cell culture artifact.
f HA numbering begins after the predicted signal peptide.

Zoonotic Viruses: Substitutions conferring reduced susceptibility to zanamivir have been observed in viruses with zoonotic potential (Table 8). The clinical impact of reduced susceptibility in these viruses is unknown, and the effects of specific substitutions on virus susceptibility to zanamivir may be strain-dependent.

Table 8: Amino Acid Substitutions Observed in Avian Influenza Viruses with Zoonotic Potential and Associated with Reduced Susceptibility to Zanamivir
Protein | Type/Subtype
Protein | A/H5N1a (N2 numberingb) | A/H7N9c (N2 numberingb)
NA | V96A (116), E99A/Gd (119), Q116Ld (136), V129Ae (149), D179G (198), N275S (294)+T418N (439), K412E/T (432), T418I/N (439) | E115Ve (119), R148Ke (152), I219K/Re (222), R289Ke (292)
NA = Neuraminidase.
a Numbering based on A/Vietnam/1203/2004.
b N2 numbering based on A/Texas/50/2012.
c Numbering based on A/Anhui/1/2013.
d Selected in cell culture or animal models of influenza.
e Observed in virus isolated from humans.

Circulating resistant variants may change from season to season. Prescribers should consider available information from the U.S. Centers for Disease Control and Prevention regarding influenza virus drug susceptibility patterns and treatment effects when deciding whether to use zanamivir.

Cross-Resistance

Cross-resistance between zanamivir and oseltamivir or peramivir has been observed in neuraminidase inhibition assays and cell culture assays. The NA amino acid substitutions that have been shown to result in reduced susceptibility to zanamivir and either oseltamivir or peramivir are summarized in Table 9. HA substitutions associated with reduced susceptibility to zanamivir may reduce susceptibility to all NAIs. The clinical impact of substitutions associated with reduced susceptibility to zanamivir and other NAIs is variable and may be strain-dependent.

Table 9: Zanamivir Resistance-Associated Neuraminidase Substitutions Observed in Virus from Humans and Conferring Cross-Resistance to Oseltamivir or Peramivir in Susceptibility Assays
Neuraminidase Inhibitor | Type/Subtype
Neuraminidase Inhibitor | A/H1N1a | A/H3N2b | Bc
Oseltamivir | S110F, V116A, E119D/G, H126N, D151Gd+H275Y, R152K, Y155H, D199G/Y, I223R/K/T, S247R, I267V, Q313R, N325K, R368K, I427T | E119I/V, D151V, ∆245-248e, R292K, N294S, V303I, G320R, N329K/R, S333G, N342K, Q391K, D463N | P76S, G104E, E105K, G108E, E117D/G, H134R, P139S, G140R, R150K, D197E/N/Y, A200T, I221L/N/T, G243D/S, A245T, I348T, R374K, G407S, H431R, W438R
Peramivir | E119D/G, H126N, Q136Kd, D151Gd+H275Y, D199G, I223R/K, S247R, I427T | E119I/V, Q136Kd, D151A/Gd/V, R292K, N342K, Q391K, D463N | G104E, E105K, G108E, E117G, H134N/R, Q138R, P139S, G140R, G145R, D197E/N/Y, A200T, I221L/N/T, G243S, A245T, G247D+I361V, R374K, G407S, H431R, W438R
a Numbering based on A/California/04/2009.
b Numbering based on A/Texas/50/2012.
c Numbering based on B/Massachusetts/02/2012.
d Possible cell culture artifact.
e Deletion of amino acids SASG.

Influenza Vaccine Interaction Trial

An interaction trial (n = 138) was conducted to evaluate the effects of zanamivir (10 mg once daily) on the serological response to a single dose of trivalent inactivated influenza vaccine, as measured by hemagglutination inhibition titers. There was no difference in hemagglutination inhibition antibody titers at 2 weeks and 4 weeks after vaccine administration between zanamivir and placebo recipients.

13 NONCLINICAL TOXICOLOGY

13.1 Carcinogenesis, Mutagenesis, Impairment of Fertility

Carcinogenesis

In 2-year carcinogenicity studies conducted in rats and mice using a powder formulation administered through inhalation, zanamivir induced no statistically significant increases in tumors over controls. The maximum daily exposures in rats and mice were approximately 23 to 25 and 20 to 22 times, respectively, greater than those in humans at the proposed clinical dose based on AUC comparisons.

Mutagenesis

Zanamivir was not mutagenic in in vitro and in vivo genotoxicity assays which included bacterial mutation assays in S. typhimurium and E. coli, mammalian mutation assays in mouse lymphoma, chromosomal aberration assays in human peripheral blood lymphocytes, and the in vivo mouse bone marrow micronucleus assay.

Impairment of Fertility

Zanamivir did not impair mating or fertility of male or female rats and did not affect the sperm of treated male rats dosed for 10 weeks prior to mating and throughout mating, gestation/lactation, and shortly after weaning, and female rats dosed for 3 weeks prior to mating through organogenesis or lactation, at intravenous (IV) doses 1, 9, and 90 mg/kg/day, resulting in systemic drug exposures (AUC) estimated to be up to 300 times higher than the MRHID.

14 CLINICAL STUDIES

14.1 Treatment of Influenza

Adults and Adolescents

The efficacy of RELENZA 10 mg inhaled twice daily for 5 days in the treatment of influenza has been evaluated in placebo-controlled trials conducted in North America, the Southern Hemisphere, and Europe during their respective influenza seasons. The magnitude of treatment effect varied between trials, with possible relationships to population-related factors including amount of symptomatic relief medication used.

Populations Studied: The principal Phase 3 trials enrolled 1,588 subjects aged 12 years and older (median age 34 years, 49% male, 91% Caucasian), with uncomplicated influenza-like illness within 2 days of symptom onset. Influenza was confirmed by culture, hemagglutination inhibition antibodies, or investigational direct tests. Of 1,164 subjects with confirmed influenza, 89% had influenza A and 11% had influenza B. These trials served as the principal basis for efficacy evaluation, with more limited Phase 2 studies providing supporting information where necessary. Following randomization to either zanamivir or placebo (inhaled lactose vehicle), all subjects received instruction and supervision by a healthcare professional for the initial dose.

Principal Results: The definition of time to improvement in major symptoms of influenza included no fever and self-assessment of “none” or “mild” for headache, myalgia, cough, and sore throat. A Phase 2 and a Phase 3 trial conducted in North America (total of over 600 influenza-positive subjects) suggested up to 1 day of shortening of median time to this defined improvement in symptoms in subjects receiving zanamivir compared with placebo, although statistical significance was not reached in either of these trials. In a trial conducted in the Southern Hemisphere (321 influenza-positive subjects), a 1.5-day difference in median time to symptom improvement was observed. Additional evidence of efficacy was provided by the European trial.

Other Findings: There was no consistent difference in treatment effect in subjects with influenza A compared with influenza B; however, these trials enrolled smaller numbers of subjects with influenza B and thus provided less evidence in support of efficacy in influenza B.

In general, subjects with lower temperature (e.g., 38.2°C or less) or investigator-rated as having less severe symptoms at entry derived less benefit from therapy.

No consistent treatment effect was demonstrated in subjects with underlying chronic medical conditions, including respiratory or cardiovascular disease [see Warnings and Precautions (5.4)].

No consistent differences in rate of development of complications were observed between treatment groups.

Some fluctuation of symptoms was observed after the primary trial endpoint in both treatment groups.

Pediatric Patients

The efficacy of RELENZA 10 mg inhaled twice daily for 5 days in the treatment of influenza in pediatric patients has been evaluated in a placebo-controlled trial conducted in North America and Europe, enrolling 471 subjects, aged 5 to 12 years (55% male, 90% Caucasian), within 36 hours of symptom onset. Of 346 subjects with confirmed influenza, 65% had influenza A and 35% had influenza B. The definition of time to improvement included no fever and parental assessment of no or mild cough and absent/minimal muscle and joint aches or pains, sore throat, chills/feverishness, and headache. Median time to symptom improvement was 1 day shorter in subjects receiving zanamivir compared with placebo. No consistent differences in rate of development of complications were observed between treatment groups. Some fluctuation of symptoms was observed after the primary trial endpoint in both treatment groups.

Although this trial was designed to enroll children aged 5 to 12 years, the product is indicated only for children aged 7 years and older. This evaluation is based on the combination of lower estimates of treatment effect in 5- and 6-year-olds compared with the overall trial population, and evidence of inadequate inhalation through the DISKHALER in a pharmacokinetic trial [see Use in Specific Populations (8.4), Clinical Pharmacology (12.3)].

14.2 Prophylaxis of Influenza

The efficacy of RELENZA in preventing naturally occurring influenza illness has been demonstrated in 2 post-exposure prophylaxis trials in households and 2 seasonal prophylaxis trials during community outbreaks of influenza. The primary efficacy endpoint in these trials was the incidence of symptomatic, laboratory-confirmed influenza, defined as the presence of 2 or more of the following symptoms: oral temperature greater than or equal to 100°F/37.8°C or feverishness, cough, headache, sore throat, and myalgia; and laboratory confirmation of influenza A or B by culture, PCR, or seroconversion (defined as a 4-fold increase in convalescent antibody titer from baseline).

Household Prophylaxis Trials

Two trials assessed post-exposure prophylaxis in household contacts of an index case. Within 1.5 days of onset of symptoms in an index case, each household (including all family members aged 5 years and older) was randomized to RELENZA 10 mg inhaled once daily or placebo inhaled once daily for 10 days. In the first trial only, each index case was randomized to RELENZA 10 mg inhaled twice daily for 5 days or inhaled placebo twice daily for 5 days. In this trial, the proportion of households with at least 1 new case of symptomatic laboratory-confirmed influenza was reduced from 19.0% (32 of 168 households) for the placebo group to 4.1% (7 of 169 households) for the group receiving RELENZA.

In the second trial, index cases were not treated. The incidence of symptomatic laboratory-confirmed influenza was reduced from 19.0% (46 of 242 households) for the placebo group to 4.1% (10 of 245 households) for the group receiving RELENZA.

Seasonal Prophylaxis Trials

Two seasonal prophylaxis trials assessed RELENZA 10 mg inhaled once daily versus placebo inhaled once daily for 28 days during community outbreaks. The first trial enrolled subjects aged 18 years or older (mean age: 29 years) from 2 university communities. The majority of subjects were unvaccinated (86%). In this trial, the incidence of symptomatic laboratory-confirmed influenza was reduced from 6.1% (34 of 554) for the placebo group to 2.0% (11 of 553) for the group receiving RELENZA.

The second seasonal prophylaxis trial enrolled subjects aged 12 to 94 years (mean age: 60 years) with 56% of them older than 65 years. Sixty-seven percent of the subjects were vaccinated. In this trial, the incidence of symptomatic laboratory-confirmed influenza was reduced from 1.4% (23 of 1,685) for the placebo group to 0.2% (4 of 1,678) for the group receiving RELENZA.

16 HOW SUPPLIED/STORAGE AND HANDLING

RELENZA is supplied in a circular double-foil pack (a ROTADISK) containing 4 blisters of the drug. Five ROTADISKs are packaged in a white polypropylene tube. The tube is packaged in a carton with 1 blue and gray DISKHALER inhalation device (NDC 0173-0681-01).

Store at 25°C (77°F); excursions permitted to 15° to 30°C (59° to 86°F) (see USP Controlled Room Temperature). Keep out of reach of children. Do not puncture any RELENZA ROTADISK blister until taking a dose using the DISKHALER.

17 PATIENT COUNSELING INFORMATION

Advise the patient to read the FDA-approved patient labeling (Patient Information and Instructions for Use).

Bronchospasm

Inform patients of the risk of bronchospasm, especially in the setting of underlying airways disease, and advise patients to stop RELENZA and contact their healthcare provider if they experience increased respiratory symptoms during treatment such as worsening wheezing, shortness of breath, or other signs or symptoms of bronchospasm [see Warnings and Precautions (5.1)]. If a decision is made to prescribe RELENZA for a patient with asthma or chronic obstructive pulmonary disease, the patient should be made aware of the risks and should have a fast-acting bronchodilator available.

Concomitant Bronchodilator Use

Patients scheduled to take inhaled bronchodilators at the same time as RELENZA should be advised to use their bronchodilators before taking RELENZA.

Neuropsychiatric Events

Inform patients with influenza (the flu), particularly children and adolescents, they may be at an increased risk of seizures, confusion, or abnormal behavior early in their illness. These events may occur after beginning RELENZA or may occur when flu is not treated. These events are uncommon but may result in accidental injury to the patient. Therefore, patients should be observed for signs of unusual behavior and a healthcare professional should be contacted immediately if the patient shows any signs of unusual behavior [see Warnings and Precautions (5.3)].

Risk of Influenza Transmission to Others

Inform patients that the use of RELENZA for treatment of influenza has not been shown to reduce the risk of transmission of influenza to others.

Missed Dose

Instruct patients that if they miss a dose of RELENZA, to take it as soon as they remember. If it is 2 hours or less before their next dose, instruct patients not to take the missed dose and to take the next dose of RELENZA at the next scheduled time. Advise patients not to double their next dose or take more than the prescribed dose.

Instructions for Use

Instruct patients in use of the delivery system. Instructions should include a demonstration whenever possible. For the proper use of RELENZA, the patient should read and follow carefully the accompanying Instructions for Use.

If RELENZA is prescribed for children, it should be used only under adult supervision and instruction, and the supervising adult should first be instructed by a healthcare professional [see Dosage and Administration (2.1)].

Trademarks are owned by or licensed to the GSK group of companies.

GlaxoSmithKline

Durham, NC 27701

©2023 GSK group of companies or its licensor.

RLZ:14PI

PATIENT INFORMATION

RELENZA (ruh-LENS-uh)

(zanamivir inhalation powder)

for oral inhalation use

What is RELENZA?

RELENZA is a prescription medicine used to:

- treat the flu (influenza A and B virus) in people who are aged 7 years and older who have had flu symptoms for no more than 2 days.
- help prevent the flu in people who are aged 5 years and older.

RELENZA is not recommended for the treatment or prevention of the flu in people with breathing problems, such as asthma and chronic obstructive pulmonary disease (COPD).

RELENZA does not treat or prevent illness that is caused by infections other than the influenza virus (A and B).

Using RELENZA for the treatment of the flu has not been shown to reduce the risk of spreading the flu to others.

It is not known if RELENZA is:

- effective for the treatment of flu in people with breathing problems.
- effective for the prevention of flu in people who live in nursing homes.
- safe and effective for the treatment of flu in children younger than 7 years.
- safe and effective for the prevention of flu in children younger than 5 years.

RELENZA does not take the place of receiving a flu vaccination. Talk to your healthcare provider about when you should receive an annual flu vaccination.

Do not take RELENZA if you are allergic to zanamivir or any other ingredient of RELENZA, including milk proteins. See the end of this Patient Information leaflet for a complete list of ingredients in RELENZA.

Before taking RELENZA, tell your healthcare provider about all of your medical conditions, including if you:

- have any breathing problems, such as asthma or COPD.
- received live attenuated influenza vaccine (LAIV) in your nose (intranasal) in the past 2 weeks.
- are pregnant or plan to become pregnant.
- are breastfeeding or plan to breastfeed. It is not known if RELENZA passes into your breast milk.

Tell your healthcare provider about all the medicines you take, including prescription and over-the-counter medicines, vitamins, and herbal supplements.

How should I take RELENZA?

Read the Instructions for Use at the end of this Patient Information for detailed information on how to take RELENZA.

- Take RELENZA exactly as your healthcare provider tells you to.
- RELENZA is taken by oral inhalation using a DISKHALER.
- If you are scheduled to use an inhaled bronchodilator at the same time as RELENZA, use the inhaled bronchodilator before taking RELENZA.
- Each dose of RELENZA requires 2 inhalations. Each inhalation requires 1 blister.

For the treatment of flu in people aged 7 years and older, take RELENZA as follows:

- Take each dose of RELENZA as 2 inhalations (use 1 blister per inhalation) 2 times a day for 5 days.
- On the first day, wait at least 2 hours between each dose.
- Starting on the second day, wait at least 12 hours between each dose.

To help prevent the flu in people aged 5 years and older, take RELENZA as follows:

- Take each dose of RELENZA as 2 inhalations (use 1 blister per inhalation) 1 time each day for 10 or 28 days as prescribed by your healthcare provider.
- Take RELENZA at the same time each day.

If you miss a dose of RELENZA, take it as soon as you remember. If it is 2 hours or less before your next dose, do not take the missed dose. Take your next dose of RELENZA at your scheduled time. Do not take 2 doses at the same time.

What are the possible side effects of RELENZA?

RELENZA can cause serious side effects, including:

- Bronchospasm (wheezing). Serious breathing problems, including death, have happened during treatment with RELENZA in people with and without a history of breathing problems. Stop taking RELENZA and get emergency medical help right away if you develop:

- worsening breathing
- shortness of breath

- chest pain or tightness
- cough

- If you have breathing problems, such as asthma and COPD and your healthcare provider has prescribed RELENZA, you should have a fast‑acting, inhaled bronchodilator available for your use. See “How should I take RELENZA?”
- Serious allergic reactions. RELENZA can cause serious allergic reactions. Stop taking RELENZA and get emergency medical help right away if you get any of the following symptoms:

- skin rash or hives
- your skin blisters and peels
- blisters or sores in your mouth
- itching

- swelling of your face, eyes, lips, tongue, or throat
- trouble breathing
- chest pain or tightness

- Change in behavior. People, especially children, who have the flu, can develop nervous system problems and abnormal behavior that can lead to death. During treatment with RELENZA, tell your healthcare provider right away if you or your child have confusion, speech problems, shaky movements, seizures, or start hearing voices or seeing things that are not really there (hallucinations).

The most common side effects of RELENZA include:

- headaches
- diarrhea
- nausea
- vomiting
- irritation of the nose

- airway irritation (bronchitis)
- cough
- sinusitis
- ear, nose, and throat infections
- dizziness

Other kinds of infections can appear like flu or happen along with flu, and may need different kinds of treatment. Call your healthcare provider if you feel worse or develop new symptoms during or after treatment with RELENZA, or if your flu symptoms do not start to get better.

These are not all of the possible side effects of RELENZA.

Call your doctor for medical advice about side effects. You may report side effects to FDA at 1‑800‑FDA‑1088.

How should I store RELENZA?

- Store RELENZA at room temperature below 77°F (25°C).
- Do not puncture any RELENZA ROTADISK blister until you are ready to take your dose using the DISKHALER.

Keep RELENZA and all medicines out of the reach of children.

General information about the safe and effective use of RELENZA.

Medicines are sometimes prescribed for purposes other than those listed in a Patient Information leaflet. Do not use RELENZA for a condition for which it was not prescribed. Do not give RELENZA to other people, even if they have the same symptoms that you have. It may harm them. You can ask your healthcare provider or pharmacist for information about RELENZA that is written for health professionals.

What are the ingredients in RELENZA?

Active ingredient: zanamivir

Inactive ingredients: lactose (which contains milk proteins)

GlaxoSmithKline

Durham, NC 27701

Trademarks are owned by or licensed to the GSK group of companies.

©2023 GSK group of companies or its licensor.

RLZ:9PIL

For more information call -1-888-825-5249.

This Patient Information has been approved by the U.S. Food and Drug Administration.

Revised: 10/2023

INSTRUCTIONS FOR USE
RELENZA (ruh-LENS-uh)
(zanamivir inhalation powder)
for oral inhalation use

Read the Patient Information and this Instructions for Use before you start using RELENZA.

Important information:

- Be sure to take the dose of RELENZA your healthcare provider has prescribed.
- If RELENZA is prescribed for a child, the dose should be given or supervised by an adult who has been instructed on how to use the DISKHALER the right way by a healthcare provider and understands how to use it.
- Always check inside the mouthpiece to make sure it is clear before each use. If foreign objects are in the mouthpiece, they could be inhaled and cause serious harm.
- Always replace the cover after each use.
- Throw away the DISKHALER after treatment is completed.
- RELENZA is not in a child-proof container.

Step-by-step instructions for using the DISKHALER:

Step 1: Load the medicine into the DISKHALER.

Figure A

- Start by pulling off the blue cover. See Figure A.
- Always check inside the mouthpiece to make sure it is clear before each use. If foreign objects are in the mouthpiece, they could be inhaled and cause serious harm.

Figure B

- Pull the white mouthpiece by the edges to extend the white tray all the way. See Figure B.

Figure C

- Once the white tray is extended all the way, find the raised ridges on each side of it. Press in these ridges, both sides at the same time, and pull the whole white tray out of the DISKHALER body. See Figure C.

Figure D

- Place one silver medicine disk onto the dark brown wheel, flat side up. The four silver blisters on the underside of the medicine disk will drop neatly into the four holes in the wheel. See Figure D.

Figure E

- Push in the white tray as far as it will go. Now the DISKHALER is loaded with medicine. See Figure E.

Step 2: Puncture the blister.
The DISKHALER punctures 1 blister of medicine at a time so you can inhale the right amount. It does not matter which blister you start with. Check to make sure that the silver foil is not broken.

Figure F

- Be sure to keep the DISKHALER level so the medicine does not spill out. See Figure F.

Figure G

- Locate the half-circle flap with the name “RELENZA” on top of the DISKHALER.
- Lift this flap from the outer edge until it cannot go any farther. Flap must be straight up for the plastic needle to puncture both the top and bottom of the silver medicine disk inside. See Figure G.

Figure H

- Keeping the DISKHALER level, click the flap down into place. See Figure H.

Step 3: Inhale.

Figure I

- Before putting the white mouthpiece into your mouth, breathe all the way out (exhale). See Figure I.
Then put the white mouthpiece into your mouth. Be sure to keep the DISKHALER level so the medicine does not spill out.
- Close your lips firmly around the mouthpiece. Be sure not to cover the small holes on either side of it. See Figure J.
- Breathe in through your mouth steadily and as deeply as you can. Your breath pulls the medicine into your airways and lungs.
- Hold your breath for a few seconds to help RELENZA stay in your lungs where it can work.

Figure J

To take another inhalation, move to the next blister by following Step 4 below.

After you have inhaled the number of blisters prescribed by your healthcare provider, replace the cover until your next dose.

Step 4: Move the medicine disk to the next blister.

Figure K

- Pull the mouthpiece to extend the white tray, without removing it. See Figure K.

Figure L

- Then push it back until it clicks. This pull-push motion rotates the medicine disk to the next blister. See Figure L.
- To take your next inhalation, repeat Steps 2 and 3.

If all 4 blisters in the medicine disk have been used, you are ready to start a new medicine disk (see Step 1). Check to make sure that the silver foil is not broken each time you are ready to puncture the next blister.

Trademarks are owned by or licensed to the GSK group of companies.
GlaxoSmithKline

Durham, NC 27701

©2023 GSK group of companies or its licensor.

RLZ:2IFU

This Instructions for Use has been approved by the U.S. Food and Drug Administration. Revised: 10/2023

PACKAGE LABEL

PRINCIPAL DISPLAY PANEL

NDC 0173-0681-01

RELENZA

(ZANAMIVIR) INHALATION POWDER

20 mg per Rotadisk

(5 mg per blister)

Each blister contains 5 mg zanamivir with lactose.

Use RELENZA with DISKHALER inhalation device only.

See enclosed “Patient Information” and “Patient Instructions for Use.”

Store at 25oC (77oF); excursions permitted to 15o to 30oC (59o to 86oF) (see USP Controlled Room Temperature).

Do not accept if glued carton seals are broken.

Contains 5 RELENZA ROTADISKS each containing four 5-mg blisters and one DISKHALER inhalation device.

Rx only

See prescribing information for dosage information.

20 blisters

FOR ORAL INHALATION ONLY

GSK

Made in UK

©2024 the GSK group of companies

Rev. 1/24

62000000091644